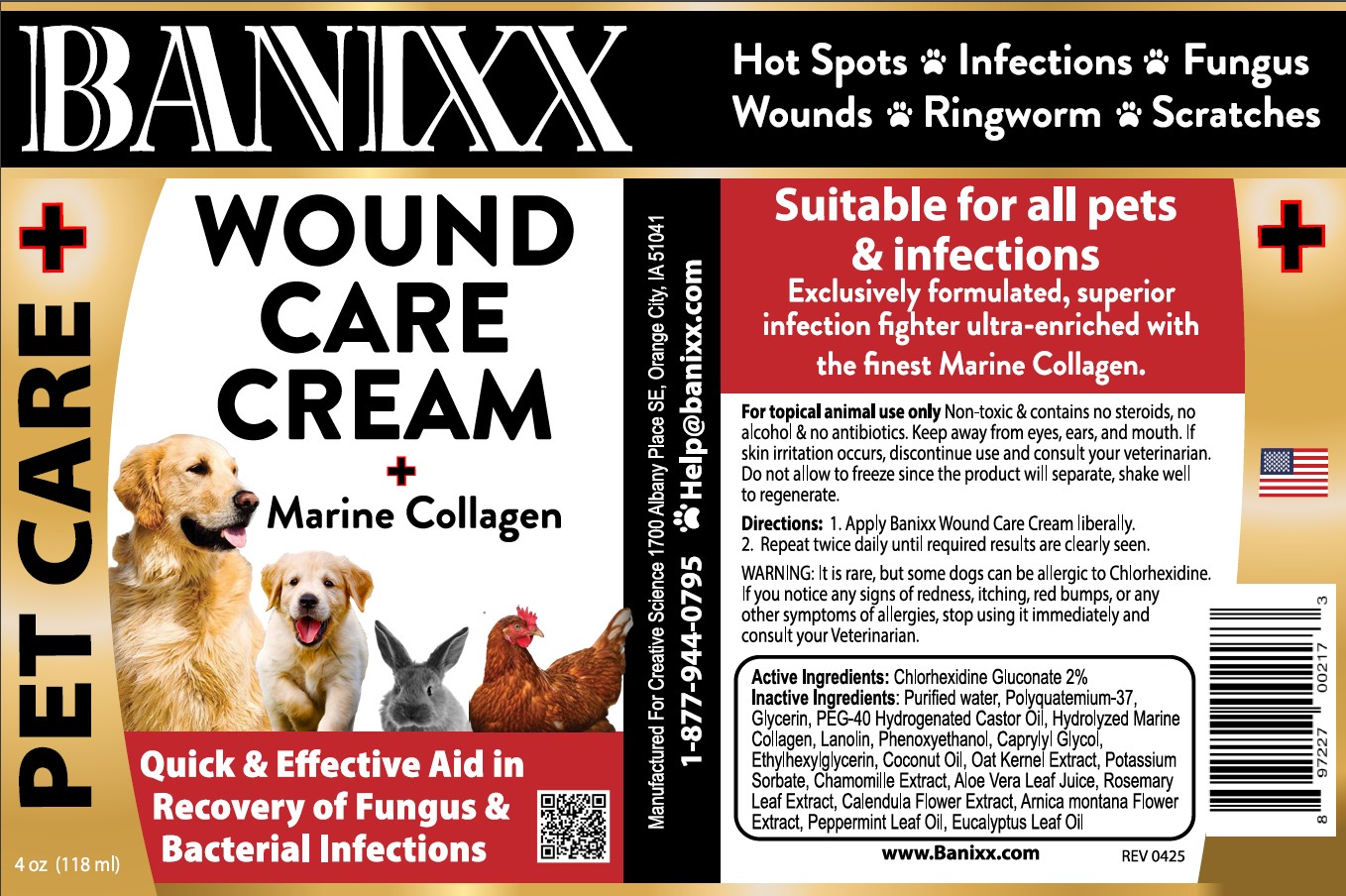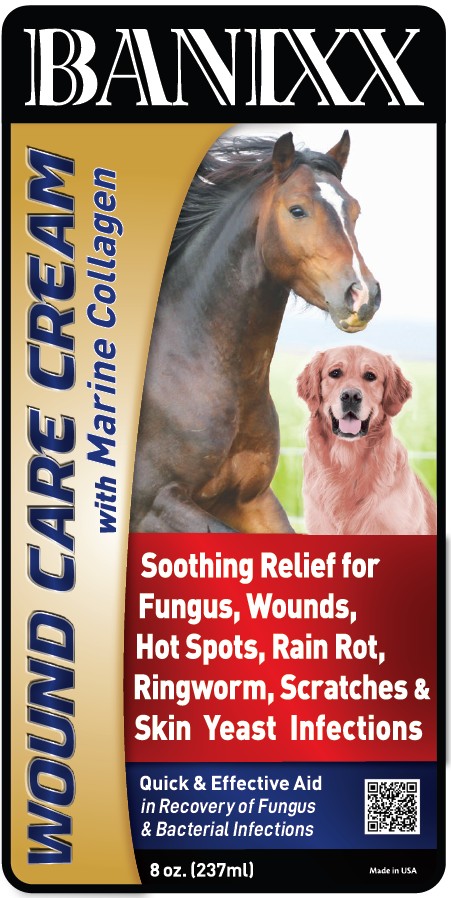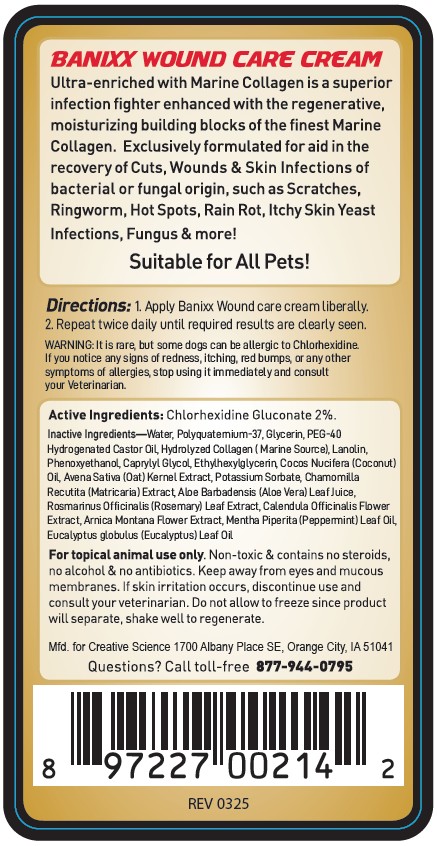 DRUG LABEL: Banixx Wound Care Cream with Marine Collagen
NDC: 86099-208 | Form: CREAM
Manufacturer: Creative Science
Category: animal | Type: OTC ANIMAL DRUG LABEL
Date: 20251121

ACTIVE INGREDIENTS: CHLORHEXIDINE GLUCONATE 20 mg/1 mL

BANIXX WOUND CARE CREAM with Marine Collagen

Active Ingredients—Chlorhexidine Gluconate 2%.

PURPOSE

Quick and Effective Aid in the Recovery of Fungus and Bacterial Infections

INDICATIONS AND USAGE

Ultra-enriched with Marine Collagen is a superior infection fighter enhanced with the regenerative, moisturizing building blocks of the finest Marine Collagen. Exclusively formulated for aid in the recovery of Cuts, Wounds & Skin Infections of bacterial or fungal origin, such as Scratches, Ringworm, Hot Spots, Rain Rot, Itchy Skin Yeast Infections, Fungus & more!

Suitable for All Pets!

WARNINGS

For topical animal use only. Non-toxic & contains no steroids, no alcohol & no antibiotics. Keep away from eyes and mucous membranes. If skin irritation occurs, discontinue use and consult your veterinarian. Do not allow to freeze since the product will separate, shake well to regenerate.

Directions:

1. Apply Banixx Wound Care cream liberally.

2. Repeat twice daily until required results are clearly seen.

INACTIVE INGREDIENT

Inactive Ingredients—Water, Polyquaternium-37, Glycerin, PEG-40 Hydrogenated Castor Oil, Hydrolyzed Collagen (Marine Source), Lanolin, Phenoxyethanol, Caprylyl Glycol, Ethylhexylglycerin, Coconut Oil, Oat Kernel Extract, Potassium Sorbate, Matricaria Extract, Aloe Vera Leaf Juice, Rosemary Leaf Extract, Calendula Officinalis Flower Extract, Arnica Montana Flower Extract, Peppermint Leaf Oil, Eucalyptus Leaf Oil

Questions? Call toll-free 877-944-0795

Soothing Relief for Fungus, Wounds, Hot Spots, Rain Rot, Ringworm, Scratches & Skin Yeast Infections

Made in USA

Distributed by Creative Science 1700 Albany Place SE Orange City, IA 51041